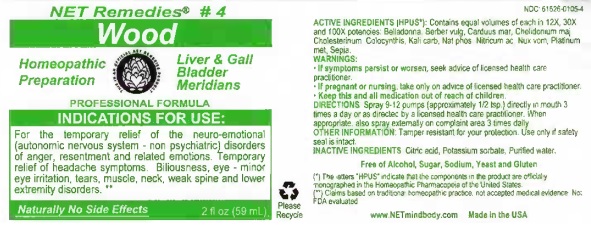 DRUG LABEL: Wood
NDC: 61626-0105 | Form: LIQUID
Manufacturer: NET Remedies
Category: homeopathic | Type: HUMAN OTC DRUG LABEL
Date: 20210119

ACTIVE INGREDIENTS: ATROPA BELLADONNA 12 [hp_X]/59 mL; BERBERIS VULGARIS ROOT BARK 12 [hp_X]/59 mL; MILK THISTLE 12 [hp_X]/59 mL; CHELIDONIUM MAJUS 12 [hp_X]/59 mL; CHOLESTEROL 12 [hp_X]/59 mL; CITRULLUS COLOCYNTHIS FRUIT PULP 12 [hp_X]/59 mL; POTASSIUM CARBONATE 12 [hp_X]/59 mL; SODIUM PHOSPHATE, DIBASIC, HEPTAHYDRATE 12 [hp_X]/59 mL; NITRIC ACID 12 [hp_X]/59 mL; STRYCHNOS NUX-VOMICA SEED 12 [hp_X]/59 mL; PLATINUM 12 [hp_X]/59 mL; SEPIA OFFICINALIS JUICE 12 [hp_X]/59 mL
INACTIVE INGREDIENTS: CITRIC ACID MONOHYDRATE; POTASSIUM SORBATE; WATER

Wood

ACTIVE INGREDIENT

ACTIVE INGREDIENTS (HPUS*): Contains equal volumes of each in 12X, 30X, and 100X potencies: Belladonna, Berber vulg, Carduus mar, Chelidonium maj, Cholesterinum, Colocynthis, Kali carb, Nath phos, Nitricum ac, Nux Vom, Platinum met, Sepia.

(*) The letters "HPUS" indicate that the components in the product are officially monographed in the Homeopathic Pharmacopeia of the United States.

(**) Claims based on traditional homeopathic practice, not accepted medical evidence. Not FDA evaluated.

INDICATIONS AND USAGE

INDICATIONS FOR USE: For temporary relief of the neuro-emotional (autonomic nervous system - non phychiatric) disorders of anger, resentment and related emotions. Temporary relief of headache symptoms. Billousness, eye - minor eye irritation, tears, muscle, neck, weak spine and lower extremity disorders.**

WARNINGS:

• If symptoms persist or worsen, seek advice of licensed health care practicioner.

• If pregnant or nursing, take only on advice of licensed health care practicioner.

• Keep this and all medication out of reach of children.

KEEP OUT OF REACH OF CHILDREN

• Keep this and all medication out of reach of children.

DOSAGE AND ADMINISTRATION

DIRECTIONS: Spray 9-12 pumps (approximately 1/2 tsp.) directly in mouth 3 times a day or as directed by a licensed health care practicioner. When appropriate also spray externally on complaint area 3 times daily.

OTHER INFORMATION: Tamper resistant for your protection. Use only if safety seal is intact.

INACTIVE INGREDIENTS: Citric acid, Potassium sorbate, Purifief water.

Free of Alcohol, Sugar, Sodium, Yeast and Gluten.

QUESTIONS

www.NETmindbody.com

Made in the USA

PACKAGE LABEL

NET Remedies #4

Wood

Homeopathic Preparation

Liver & Gall

Bladder Meridians

PROFESSIONAL FORMULA

Naturally No Side Effects

2 fl oz (59 mL)

PURPOSE

For temporary relief of the neuro-emotional (autonomic nervous system - non phychiatric) disorders of anger, resentment and related emotions. Temporary relief of headache symptoms. Billousness, eye - minor eye irritation, tears, muscle, neck, weak spine and lower extremity disorders.**